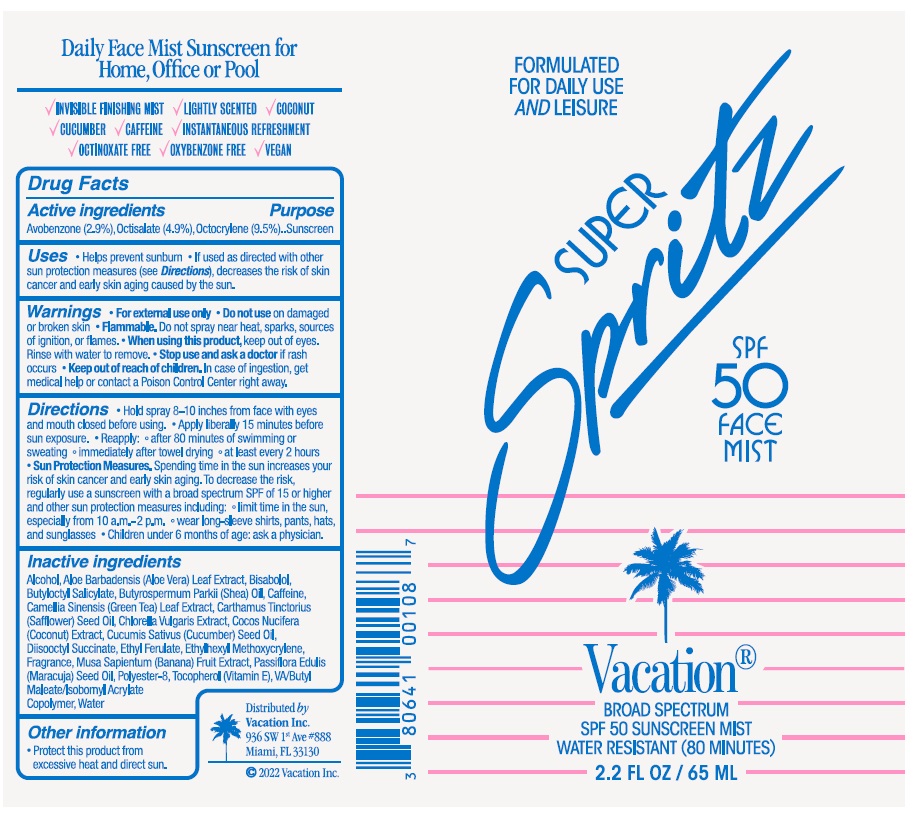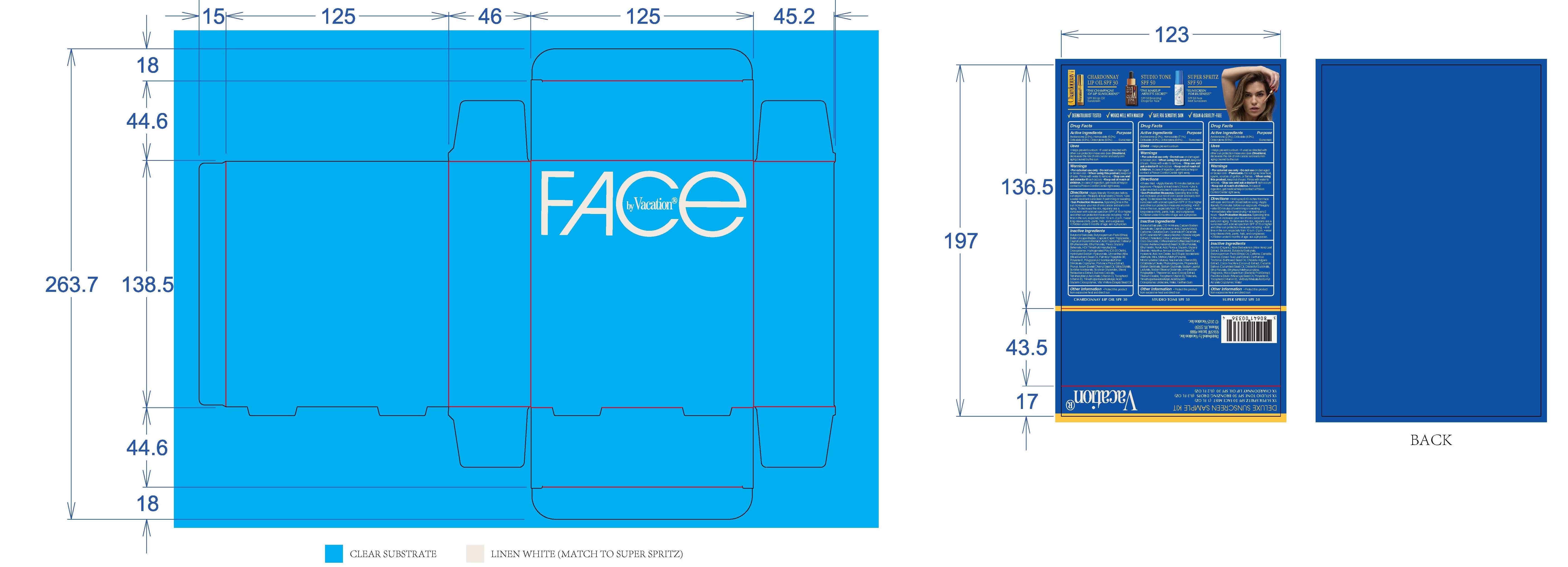 DRUG LABEL: Vacation SPF 50 Super Spritz Face Mist
NDC: 80641-010 | Form: SPRAY
Manufacturer: Vacation Inc.
Category: otc | Type: HUMAN OTC DRUG LABEL
Date: 20250220

ACTIVE INGREDIENTS: OCTOCRYLENE 9.5 g/100 mL; OCTISALATE 4.9 g/100 mL; AVOBENZONE 2.9 g/100 mL
INACTIVE INGREDIENTS: SUCCINIC ACID; ETHYL FERULATE; VINYL ACETATE; WATER; POLYESTER-8 (1400 MW, CYANODIPHENYLPROPENOYL CAPPED); SHEANUT OIL; CAFFEINE; ISOBORNYL ACRYLATE; GREEN TEA LEAF; CUCUMBER SEED OIL; COCONUT; TOCOPHEROL; DIBUTYL MALEATE; LEVOMENOL; BUTYLOCTYL SALICYLATE; ALCOHOL; ALOE VERA LEAF; SAFFLOWER OIL; CHLORELLA VULGARIS; ETHYLHEXYL METHOXYCRYLENE; BANANA; PASSIFLORA EDULIS SEED OIL

Vacation - SPF 50 Super Spritz Face Mist

ACTIVE INGREDIENT

Avobenzone (2.9%)

Homosalate (4.9%)

Octocrylene (9.5%)

PURPOSE

Sunscreen

Uses

• Helps prevent sunburn

• If used as directed with other sun protection measures (see Directions), decreases the risk of skin cancer and early skin aging caused by the sun.

WARNINGS

• For external use only

• Do not use on damaged or broken skin

• Flammable. Do not spray near heat, sparks, sources of ignition, or flames.
• When using this product, keep out of eyes. Rinse with water to remove.

• Stop use and ask a doctor if rash occurs

• Keep out of reach of children. In case of ingestion, get medical help or contact a Poison Control Center right away.

Directions

• Hold spray 8-10 inches from face with eyes and mouth closed before using

• Apply liberally 15 minutes before sun exposure.
• Reapply: • after 80 minutes of swimming or sweating. • immediately after towel drying • at least every 2 hours

• Sun Protection Measures. Spending time in the sun increases your risk of skin cancer and early skin aging. To decrease the risk, regularly use a sunscreen with a broad spectrum SPF of 15 or higher and other sun protection measures including: limit time in the sun, especially from 10 a.m. - 2 p.m. wear long-sleeve shirts, pants, hats, and sunglasses • Children under 6 months of age: ask a physician.

INACTIVE INGREDIENT

Alcohol, Aloe Barbadensis (Aloe Vera) Leaf Extract, Bisabolol, Butyloctyl Salicylate, Butyrospermum Parkii (Shea) Oil, Caffeine, Camellia Sinensis (Green Tea) Leaf Extract, Carthamus Tinctorius (Safflower) Seed Oil, Chlorella Vulgaris Extract, Cocos Nucifera (Coconut) Extract, Cucumis Sativus (Cucumber) Seed Oil, Diisooctyl Succinate, Ethyl Ferulate, Ethylhexyl Methoxycrylene, Fragrance, Musa Sapientum (Banana) Fruit Extract, Passiflora Edulis Seed Oil, Polyester-8, Tocopherol (Vitamin E), VA/Butyl Maleate/Isobornyl Acrylate Copolymer, Water

OTHER SAFETY INFORMATION

Protect this product from excessive heat and direct sun.